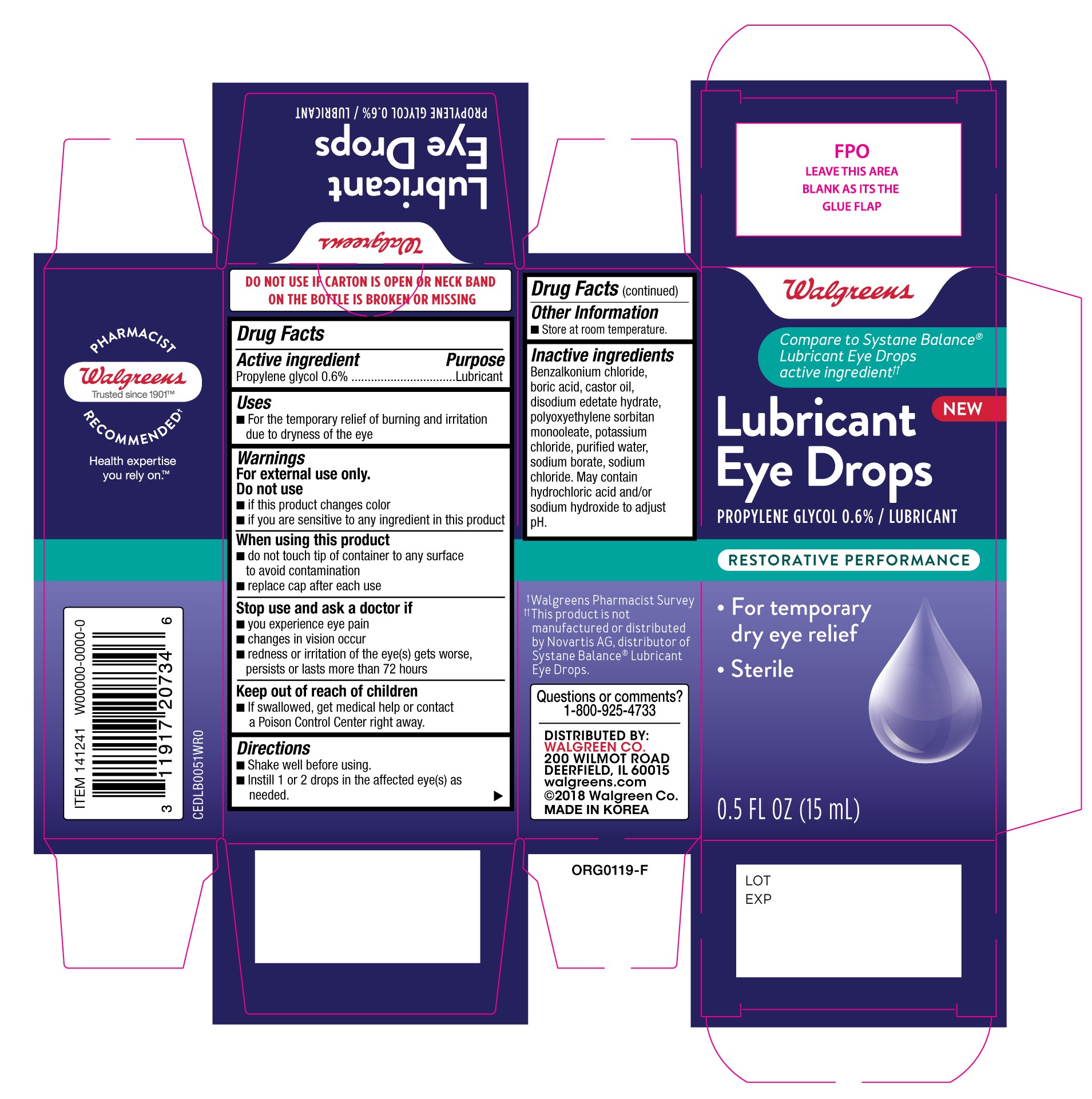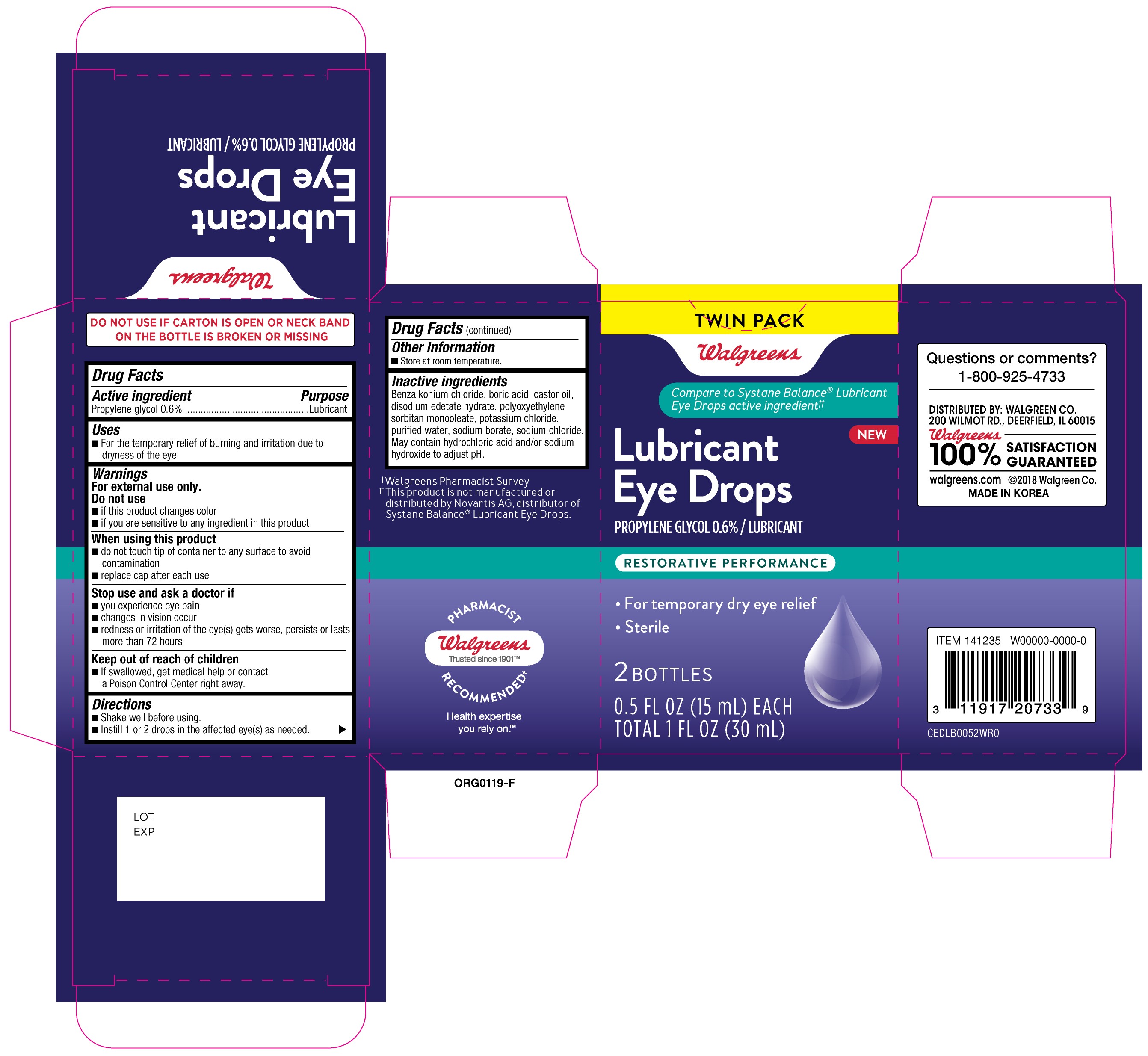 DRUG LABEL: Walgreens Lubricant Eye Drops Restorative Performance
NDC: 0363-1474 | Form: SOLUTION/ DROPS
Manufacturer: Walgreen Company
Category: otc | Type: HUMAN OTC DRUG LABEL
Date: 20231220

ACTIVE INGREDIENTS: PROPYLENE GLYCOL 0.05 g/100 mL
INACTIVE INGREDIENTS: PEG-6 SORBITAN OLEATE; EDETATE DISODIUM; POTASSIUM CHLORIDE; WATER; SODIUM BORATE; SODIUM CHLORIDE; CASTOR OIL; BENZALKONIUM CHLORIDE; BORIC ACID

Walgreens Lubricant Eye Drops Restorative Performance (PLD)

Active Ingredient

Propylene glycol 0.6%

Purpose

Lubricant

Uses

- For temporary relief of burning and irritation due to dryness of the eye

Warnings

For external use only.

Do not use

- if this product changes color
- if you are sensative to any ingredient in this product

When using this product

- do not touch tip of container to any surface to avoid contamination
- replace cap after each use

Stop use and ask a doctor if

- you experience eye pain
- changes in vision occur
- redness or irritation of the eye(s) gets worse, persists or lasts more than 72 hours

Keep out of reach of children

- if swallowed, get medical help or contact a Poison Control Center right away.

Directions

- Shake well before using.
- Instill 1 or 2 drops in the affected eye(s) as needed.

Other Information

- Store at room temperature.

Inactive ingredients

Benzalkonium chloride, boric acid, castor oil, disodium edetate hydrate, polyoxyethylene sorbitan monooleate, potassium chloride, purified water, sodium borate, sodium chloride. May contain hydrochloric acid and/or sodium hydroxide to adjust pH.

Questions or comments?

1-800-925-4733